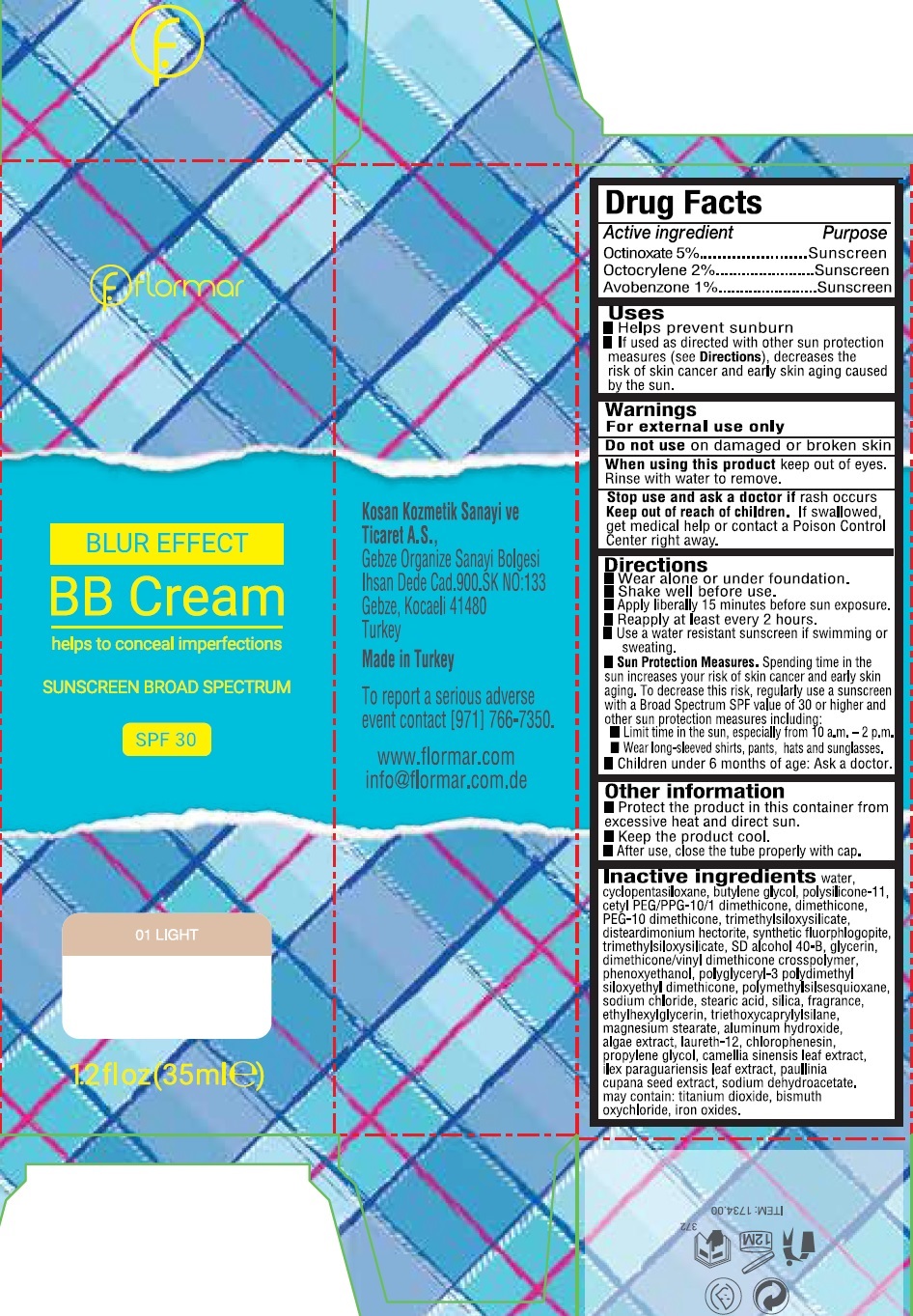 DRUG LABEL: Flormar Blur Effect BB Sunscreen Broad Spectrum SPF 30 01 Light
NDC: 61722-296 | Form: CREAM
Manufacturer: Kosan Kozmetik Sanayi ve Ticaret A.S.
Category: otc | Type: HUMAN OTC DRUG LABEL
Date: 20191018

ACTIVE INGREDIENTS: OCTINOXATE 50 mg/1 mL; OCTOCRYLENE 20 mg/1 mL; AVOBENZONE 10 mg/1 mL
INACTIVE INGREDIENTS: ETHYLHEXYLGLYCERIN; WATER; CYCLOMETHICONE 5; BUTYLENE GLYCOL; DIMETHICONE/VINYL DIMETHICONE CROSSPOLYMER (SOFT PARTICLE); DIMETHICONE; PEG-10 DIMETHICONE (600 CST); DISTEARDIMONIUM HECTORITE; GLYCERIN; PHENOXYETHANOL; SODIUM CHLORIDE; STEARIC ACID; SILICON DIOXIDE; TRIETHOXYCAPRYLYLSILANE; MAGNESIUM STEARATE; ALUMINUM HYDROXIDE; LAURETH-12; CHLORPHENESIN; PROPYLENE GLYCOL; GREEN TEA LEAF; ILEX PARAGUARIENSIS LEAF; PAULLINIA CUPANA SEED; SODIUM DEHYDROACETATE

Flormar Blur Effect BB Cream Sunscreen Broad Spectrum SPF 30 01 Light

Active ingredient

Octinoxate 5%

Octocrylene 2 %

Avobenzone 1 %

Purpose

Sunscreen

Uses

- Helps prevent sunburn
- If used as directed with other sun protection measures (see Directions), decreases the risk of skin cancer and early skin aging caused by the sun.

Warnings

For external use only

Do not use

on damaged or broken skin

When using this product

keep out of eyes. Rinse with water to remove.

Stop use and ask a doctor if

rash occurs

Keep out of reach of children.

If swallowed, get medical help or contact a Poison Control Center right away.

Directions

- Wear alone or under foundation.
- Shake well before use.
- Apply liberally 15 minutes before sun exposure.
- Reapply at least every 2 hours.
- Use a water resistant sunscreen if swimming or sweating.
- Sun Protection Measures. Spending time in the sun increases your risk of skin cancer and early skin aging. To decrease this risk, regularly use a sunscreen with a Broad Spectrum SPF value of 30 or higher and other sun protection measures including:
- Limit time in the sun, especially from 10 a.m. - 2 p.m.
- Wear long-sleeved shirts, pants, hats and sunglasses.
- Children under 6 months of age: Ask a Doctor.

Other Information

- Protect the product in this container from excessive heat and direct sun.
- Keep the product cool.
- After use, close the tube properly with cap.

Inactive ingredients

water, cyclopentasiloxane, butylene glycol, polysilicone-11, cetyl PEG/PPG-10/1 dimethicone, dimethicone, PEG-10 dimethicone, trimethylsiloxysilicate, disteardimonium hectorite, synthetic fluorphlogopite, trimethylsiloxysilicate, SD alcohol 40-B, glycerin, dimethicone/vinyl dimethicone crosspolymer, phenoxyethanol, polyglyceryl-3 polydimethyl siloxyethyl dimethicone, polymethylsilsesquioxane, sodium chloride, stearic acid, silica, fragrance, ethylhexylglycerin, triethoxycaprylylsilane, magnesium stearate, aluminum hydroxide, algae extract, laureth-12, chlorophenesin, propylene glycol, camellia sinensis leaf extract, ilex paraguariensis leaf extract, paullinia cupana seed extract, sodium dehydroacetate. may contain: titanium dioxide, bismuth oxychloride, iron oxides.